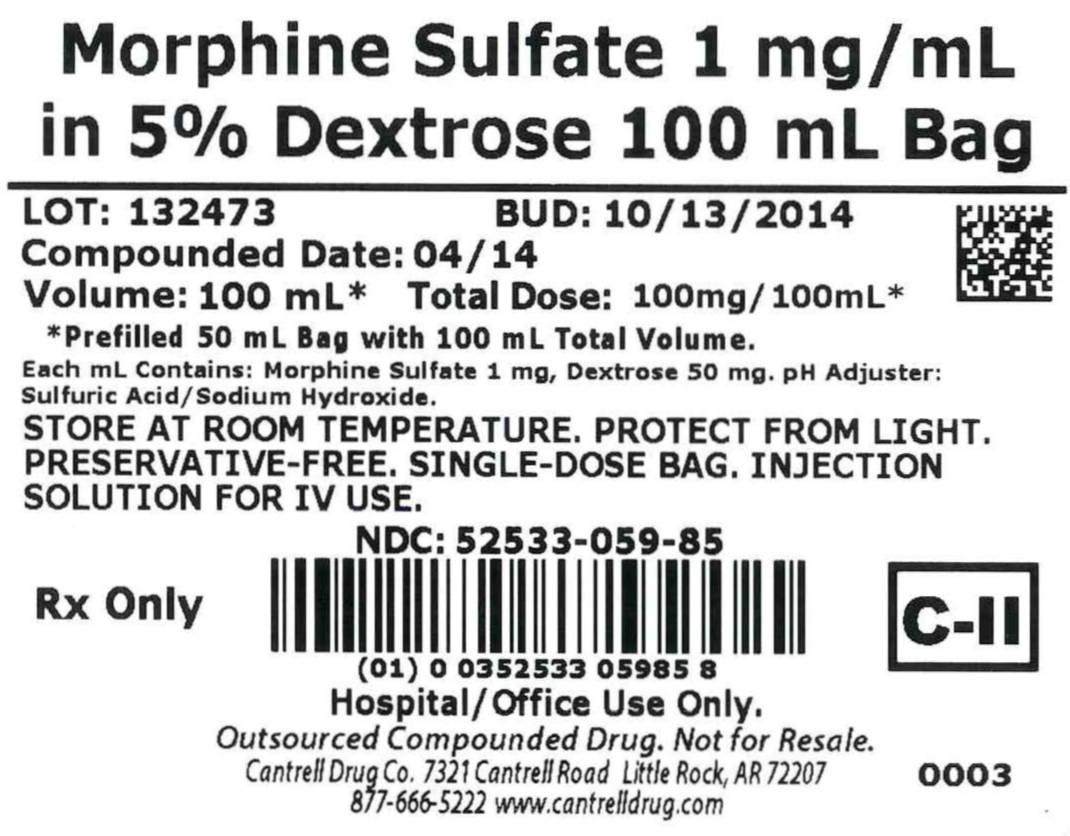 DRUG LABEL: Morphine Sulfate
NDC: 52533-059 | Form: INJECTION, SOLUTION
Manufacturer: Cantrell Drug Company
Category: prescription | Type: HUMAN PRESCRIPTION DRUG LABEL
Date: 20141020
DEA Schedule: CII

ACTIVE INGREDIENTS: Morphine Sulfate 1 mg/1 mL
INACTIVE INGREDIENTS: DEXTROSE 5 g/1 mL; Water

Morphine Sulfate 1 mg/mL in 5% Dextrose 100 mL Bag